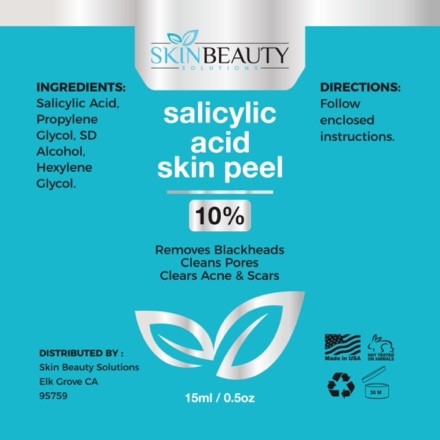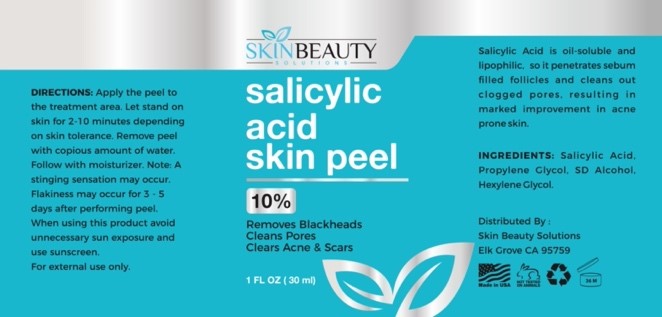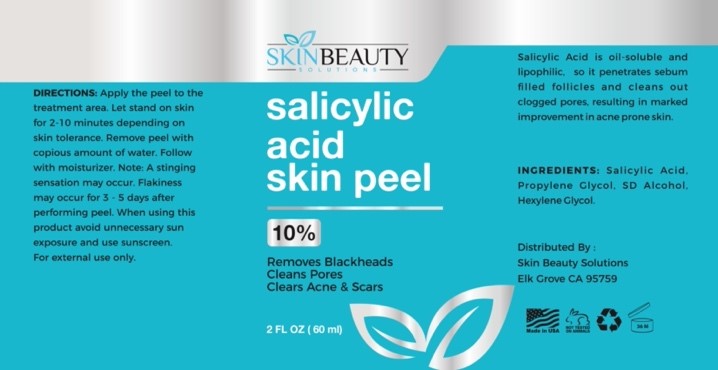 DRUG LABEL: Salicylic 10 skin peel
NDC: 84785-0012 | Form: SOLUTION
Manufacturer: Gazebo Wellness SKIN LLC
Category: otc | Type: HUMAN OTC DRUG LABEL
Date: 20241216

ACTIVE INGREDIENTS: SALICYLIC ACID 0.3 mg/30 mL
INACTIVE INGREDIENTS: HEXYLENE GLYCOL; BENZALDEHYDE PROPYLENE GLYCOL ACETAL; ALCOHOL

DOSAGE AND ADMINISTRATION

DIRECTIONS: Apply the peel to the treatment area. Let stand on skin for 2-10 minutes depending on skin tolerance. Remove peel with copious amount of water. Follow with moisturizer. Note: A stinging sensation may occur. Flakiness may occur for 3-5 days after performing peel. When using this product avoid unnecessary sun exposure and
use sunscreen
For external use only.

WARNINGS

DIRECTIONS: Apply the peel to the treatment area. Let stand on skin for 2-10 minutes depending on skin tolerance. Remove peel with copious amount of water. Follow with moisturizer. Note: A stinging sensation may occur. Flakiness may occur for 3-5 days after performing peel. When using this product avoid unnecessary sun exposure and
use sunscreen
For external use only.

Inactive ingredients: Propylene Glycol, SD Alcohol, Hexylene Glycol.

INDICATIONS AND USAGE

Apply the peel to the treatment area. Let stand on skin for 2-10 minutes depending on skin tolerance. Remove peel with copious amount of water. Follow with moisturizer. Note: A stinging sensation may occur. Flakiness may occur for 3-5 days after performing peel. When using this product avoid unnecessary sun exposure and
use sunscreen
For external use only.

keep out of reach of children

PURPOSE

salicylic acid skin peel
10%
Removes Blackheads Cleans Pores Clears Acne & Scars

Distributed By:
Skin Beauty Solutions Elk Grove CA 95759

Active ingredient: Salicylic Acid.

PACKAGE LABEL

Content of labeling